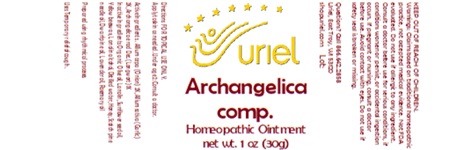 DRUG LABEL: Archangelica comp.
NDC: 48951-1391 | Form: OINTMENT
Manufacturer: Uriel Pharmacy, Inc
Category: homeopathic | Type: HUMAN OTC DRUG LABEL
Date: 20250106

ACTIVE INGREDIENTS: ONION 2 [hp_X]/1 g; ANGELICA ARCHANGELICA ROOT 1 [hp_X]/1 g; GARLIC 2 [hp_X]/1 g
INACTIVE INGREDIENTS: PINE NEEDLE OIL (PINUS MUGO); LANOLIN; ROSEMARY OIL; YELLOW WAX; PINE NEEDLE OIL (PINUS SYLVESTRIS); OLIVE OIL; SUNFLOWER OIL; WATER; LAVENDER OIL; LANOLIN ALCOHOLS; HONEY

Archangelica comp.

INDICATIONS AND USAGE

Directions: FOR TOPICAL USE ONLY.

DOSAGE AND ADMINISTRATION

Apply to skin as needed. Under age 2: Consult a doctor.

ACTIVE INGREDIENT

Active Ingredients: . Allium cepa (Onion) 2X, Allium sativa (Garlic) 2X, Archangelica e rad Dec. (Longwort) 1X

INACTIVE INGREDIENT

Inactive Ingredients: Organic Olive oil, Lanolin, Sunflower seed oil, Yellow beeswax, Lanolin alcohol, Distilled water, Honey, Scotch pine needle oil, Dwarf pine oil, Lavender oil, Rosemary oil

Prepared using rhythmical processes.

PURPOSE

Uses: Temporary relief of cough.

KEEP OUT OF REACH OF CHILDREN.

WARNINGS

Warnings: Claims based on traditional homeopathic practice, not accepted medical evidence. Not FDA evaluated. Do not use if allergic to any ingredient. Consult a doctor before use for serious conditions, if conditions worsen or persist, or accidental ingestion occurs. If pregnant or nursing, consult a doctor before use. Avoid contact with eyes. Do not use if safety seal is broken or missing.

Questions? Call 866.642.2858
Uriel, East Troy, WI 53120
shopuriel.com Lot: